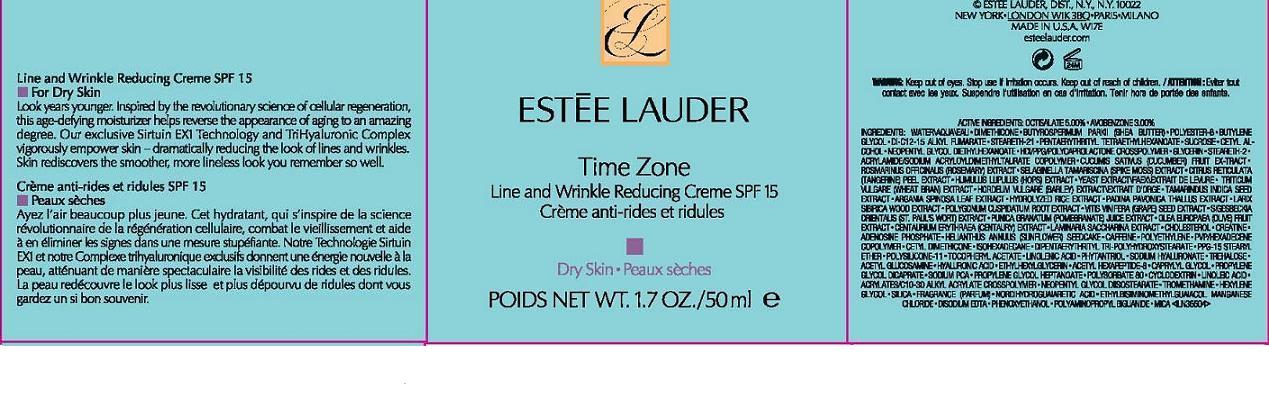 DRUG LABEL: TIME ZONE
NDC: 11559-728 | Form: CREAM
Manufacturer: ESTEE LAUDER INC
Category: otc | Type: HUMAN OTC DRUG LABEL
Date: 20110722

ACTIVE INGREDIENTS: OCTISALATE 5.0 mL/100 mL; AVOBENZONE 3.0 mL/100 mL
INACTIVE INGREDIENTS: BUTYLENE GLYCOL; GLYCERIN; DIMETHICONE; CETYL ALCOHOL; GLYCERYL MONOSTEARATE; SACCHAROMYCES LYSATE; CUCUMBER; OLIVE OIL; BARLEY; TAMARIND SEED; SACCHARINA LATISSIMA WHOLE; CHOLESTEROL; HIGH DENSITY POLYETHYLENE; LINOLEIC ACID; TREHALOSE; CREATINE; CAPRYLYL GLYCOL; POLYSORBATE 60; HYALURONATE SODIUM; SILICON DIOXIDE; CARBOMER HOMOPOLYMER TYPE C; EDETATE DISODIUM; PHENOXYETHANOL; MICA; POLYAMINOPROPYL BIGUANIDE

ACTIVE INGREDIENTS: OCTISALATE 5.00% [] AVOBENZONE 3.00%

INACTIVE INGREDIENT

INGREDIENTS: WATER\AQUA\EAU [] DIMETHICONE [] BUTYROSPERMUM PARKII (SHEA BUTTER) [] POLYESTER-8 [] BUTYLENE GLYCOL [] DI-C12-15 ALKYL FUMARATE [] STEARETH-21 [] PENTAERYTHRITYL TETRAETHYLHEXANOATE [] SUCROSE [] CETYL ALCOHOL [] NEOPENTYL GLYCOL DIETHYLHEXANOATE [] HDI/PPG/POLYCAPROLACTONE CROSSPOLYMER [] GLYCERIN [] STEARETH-2 [] ACRYLAMIDE/SODIUM ACRYLOYLDIMETHYLTAURATE COPOLYMER [] CUCUMIS SATIVUS (CUCUMBER) FRUIT EXTRACT [] ROSMARINUS OFFICINALIS (ROSEMARY) EXTRACT [] SELAGINELLA TAMARISCINA (SPIKE MOSS) EXTRACT [] CITRUS RETICULATA (TANGERINE) PEEL EXTRACT [] HUMULUS LUPULUS (HOPS) EXTRACT [] YEAST EXTRACT\FAEX\EXTRAIT DE LEVURE [] TRITICUM VULGARE (WHEAT BRAN) EXTRACT [] HORDEUM VULGARE (BARLEY) EXTRACT\EXTRAIT D'ORGE [] TAMARINDUS INDICA SEED EXTRACT [] ARGANIA SPINOSA LEAF EXTRACT [] HYDROLYZED RICE EXTRACT [] PADINA PAVONICA THALLUS EXTRACT [] LARIX SIBIRICA WOOD EXTRACT [] POLYGONUM CUSPIDATUM ROOT EXTRACT [] VITIS VINIFERA (GRAPE) SEED EXTRACT [] SIGESBECKIA ORIENTALIS (ST. PAUL'S WORT) EXTRACT [] PUNICA GRANATUM (POMEGRANATE) JUICE EXTRACT [] OLEA EUROPAEA (OLIVE) FRUIT EXTRACT [] CENTAURIUM ERYTHRAEA (CENTAURY) EXTRACT [] LAMINARIA SACCHARINA EXTRACT [] CHOLESTEROL [] CREATINE [] ADENOSINE PHOSPHATE [] HELIANTHUS ANNUUS (SUNFLOWER) SEEDCAKE [] CAFFEINE [] POLYETHYLENE [] PVP/HEXADECENE COPOLYMER [] CETYL DIMETHICONE [] ISOHEXADECANE [] DIPENTAERYTHRITYL TRI-POLYHYDROXYSTEARATE [] PPG-15 STEARYL ETHER [] POLYSILICONE-11 [] TOCOPHERYL ACETATE [] LINOLENIC ACID [] PHYTANTRIOL [] SODIUM HYALURONATE [] TREHALOSE [] ACETYL GLUCOSAMINE [] HYALURONIC ACID [] ETHYLHEXYLGLYCERIN [] ACETYL HEXAPEPTIDE-8 [] CAPRYLYL GLYCOL [] PROPYLENE GLYCOL DICAPRATE [] SODIUM PCA [] PROPYLENE GLYCOL HEPTANOATE [] POLYSORBATE 80 [] CYCLODEXTRIN [] LINOLEIC ACID [] ACRYLATES/C10-30 ALKYL ACRYLATE CROSSPOLYMER [] NEOPENTYL GLYCOL DIISOSTEARATE [] TROMETHAMINE [] HEXYLENE GLYCOL [] SILICA [] FRAGRANCE (PARFUM) [] NORDIHYDROGUAIARETIC ACID [] ETHYLBISIMINOMETHYLGUAIACOL MANGANESE CHLORIDE [] DISODIUM EDTA [] PHENOXYETHANOL [] POLYAMINOPROPYL BIGUANIDE [] MICA

WARNINGS

WARNING: KEEP OUT OF EYES. STOP USE IF IRRITATION OCCURS.

KEEP OUT OF REACH OF CHILDREN

PACKAGE LABEL

PRINCIPAL DISPLAY PANEL:
ESTEE LAUDER
TIME ZONE
LINE AND WRINKLE REDUCING CREAM
SPF 15
DRY SKIN
1.7 OZ/ 50 ML
ESTEE LAUDER DISTR.
NY, NY 10022